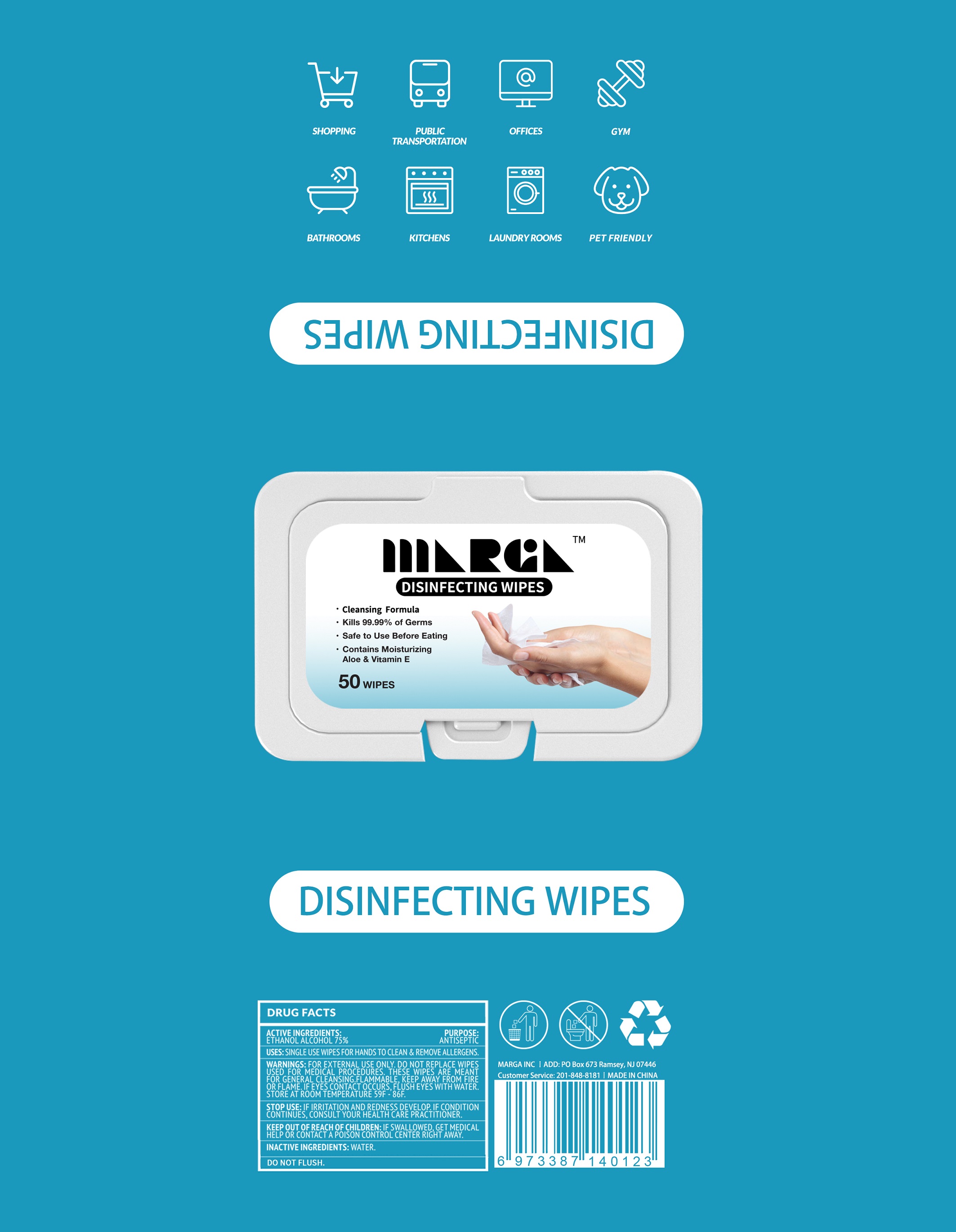 DRUG LABEL: ALCOHOL WIPES
NDC: 79323-001 | Form: CLOTH
Manufacturer: Marga Tile Inc
Category: otc | Type: HUMAN OTC DRUG LABEL
Date: 20200625

ACTIVE INGREDIENTS: ALCOHOL 3.5 mL/1 1
INACTIVE INGREDIENTS: WATER

79323-001

Active Ingredient(s)

Alcohol 75% v/v. Purpose: Antiseptic

Purpose

Daily Clean for daily items and Antimicrobial.

WHEN USING

This product is used to wipe hands, faces, skins, etc. It can also be used to clean many kinds of places.

Do not use

on children less than 2 months of age
on open skin wounds

STOP USE

IF IRRITATION AND REDNESS DEVELOP. IF CONDITION CONTINUS, CONSULT YOUR HEALTH CARE PRACTITIONER.

Keep out of reach of children.

IF SWALLOWED, GET MEDICAL HELP OR CONTACT A POISON CONTROL CENTER RIGHT AWAY.

Use

SINGLE USE WIPES FOR HANDS TO CLEAN & REMOVE ALLERGENS.

Directions

Use it as needed, after following the usage instructions.

For external use only.

Warnings

FOR EXTERNAL USE ONLY. DO NOT REPLACE WIPES USED FOR MEDICAL PROCEDURES. THESE WIPES ARE MEANT FOR GENERAL CLEANSING. FLAMMABLE , KEEP AWAY FROM FIRE OR FLAME. IF EYES CONTACT OCCURS, FLUSH EYES WITH WATER. STORE AT ROOM TEMPERATURE 59F-86F.

Other information

- Store between 15-30C (59-86F)
- Avoid freezing and excessive heat above 40C (104F)

Package Label - Principal Display Panel

50 CLOTH IN 1 BAG NDC:79323-001-01